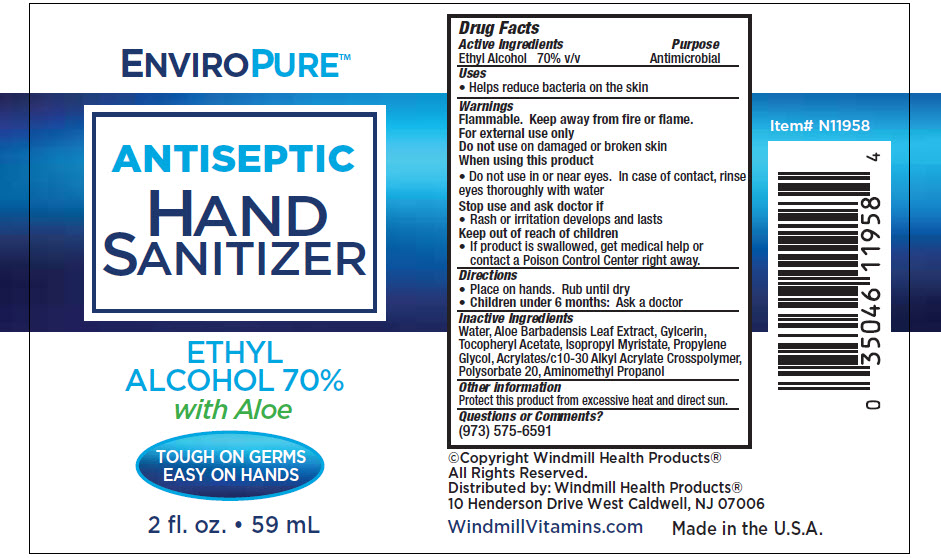 DRUG LABEL: Hand Sanitizer
NDC: 74154-007 | Form: LIQUID
Manufacturer: Windmill Health Products, LLC
Category: otc | Type: HUMAN OTC DRUG LABEL
Date: 20210715

ACTIVE INGREDIENTS: Alcohol 70 mL/100 mL
INACTIVE INGREDIENTS: Water; Aloe Vera Leaf; Glycerin; .Alpha.-Tocopherol Acetate; Isopropyl Myristate; Propylene Glycol; Carbomer Interpolymer Type A (Allyl Sucrose Crosslinked); Polysorbate 20; Aminomethylpropanol

Hand Sanitizer

Drug Facts

Active Ingredients

Ethyl Alcohol 70% v/v

Purpose

Antimicrobial

Uses

- Helps reduce bacteria on the skin

Warnings

Flammable. Keep away from fire or flame.

For external use only

Do not use on damaged or broken skin

When using this product

- Do not use in or near eyes. In case of contact, rinse eyes thoroughly with water

Stop use and ask doctor if

- Rash or irritation develops and lasts

Keep out of reach of children

- If product is swallowed, get medical help or contact a Poison Control Center right away.

Directions

- Place on hands. Rub until dry
- Children under 6 months: Ask a doctor

Inactive Ingredients

Water, Aloe Barbadensis Leaf Extract, Gylcerin, Tocopheryl Acetate, Isopropyl Myristate, Propylene Glycol, Acrylates/c10-30 Alkyl Acrylate Crosspolymer, Polysorbate 20, Aminomethyl Propanol

Other information

Protect this product from excessive heat and direct sun.

Questions or Comments?

(973) 575-6591

Distributed by: Windmill Health Products®
10 Henderson Drive West Caldwell, NJ 07006

PRINCIPAL DISPLAY PANEL - 59 mL Bottle Label

ENVIROPURE™

ANTISEPTIC

HAND
SANITIZER

ETHYL
ALCOHOL 70%
with Aloe

TOUGH ON GERMS
EASY ON HANDS

2 fl. oz. • 59 mL